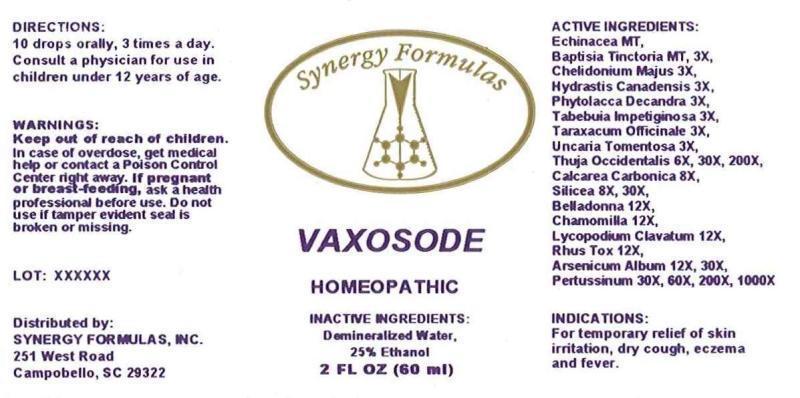 DRUG LABEL: Vaxosode
NDC: 43772-0052 | Form: LIQUID
Manufacturer: Synergy Formulas, Inc.
Category: homeopathic | Type: HUMAN OTC DRUG LABEL
Date: 20150319

ACTIVE INGREDIENTS: ECHINACEA ANGUSTIFOLIA 1 [hp_X]/1 mL; BAPTISIA TINCTORIA ROOT 1 [hp_X]/1 mL; CHELIDONIUM MAJUS 3 [hp_X]/1 mL; GOLDENSEAL 3 [hp_X]/1 mL; PHYTOLACCA AMERICANA ROOT 3 [hp_X]/1 mL; TABEBUIA IMPETIGINOSA BARK 3 [hp_X]/1 mL; TARAXACUM OFFICINALE 3 [hp_X]/1 mL; CAT'S CLAW 3 [hp_X]/1 mL; THUJA OCCIDENTALIS LEAFY TWIG 6 [hp_X]/1 mL; OYSTER SHELL CALCIUM CARBONATE, CRUDE 8 [hp_X]/1 mL; SILICON DIOXIDE 8 [hp_X]/1 mL; ATROPA BELLADONNA 12 [hp_X]/1 mL; MATRICARIA RECUTITA 12 [hp_X]/1 mL; LYCOPODIUM CLAVATUM SPORE 12 [hp_X]/1 mL; TOXICODENDRON PUBESCENS LEAF 12 [hp_X]/1 mL; ARSENIC TRIOXIDE 12 [hp_X]/1 mL; HUMAN SPUTUM, BORDETELLA PERTUSSIS INFECTED 30 [hp_X]/1 mL
INACTIVE INGREDIENTS: WATER; ALCOHOL

DRUG FACTS:

ACTIVE INGREDIENTS:

Echinacea (Angustifolia) MT, Baptisia Tinctoria MT, 3X, Chelidonium Majus 3X, Hydrastis Canadensis 3X, Phytolacca Decandra 3X, Tabebuia Impetiginosa 3X, Taraxacum Officinale 3X, Uncaria Tomentosa 3X, Thuja Occidentalis 6X, 30X, 200X, Calcarea Carbonica 8X, Silicea 8X, 30X, Belladonna 12X, Chamomilla 12X, Lycopodium Clavatum 12X, Rhus Tox 12X, Arsenicum Album 12X, 30X, Pertussinum 30X, 60X, 200X, 1000X

INDICATIONS:

For temporary relief of skin irritation, dry cough, eczema and fever.

WARNINGS:

Keep out of reach of children. In case of overdose, get medical help or contact a Poison Control Center right away.

If pregnant or breast-feeding, ask a health professional before use.

Do not use if tamper evident seal is broken or missing.

Keep out of reach of children. In case of overdose, get medical help or contact a Poison Control Center right away.

DIRECTIONS:

10 drops orally, 3 times a day. Consult a physician for use in children under 12 years of age.

INDICATIONS:

For temporary relief of skin irritation, dry cough, eczema and fever.

INACTIVE INGREDIENTS:

Demineralized Water, 25% Ethanol

QUESTIONS:

Distributed by:

SYNERGY FORMULAS, INC.

251 West Road

Campobello, SC 29322

PACKAGE LABEL DISPLAY:

Synergy Formulas

VAXOSODE

HOMEOPATHIC

2 FL OZ (60 ml)